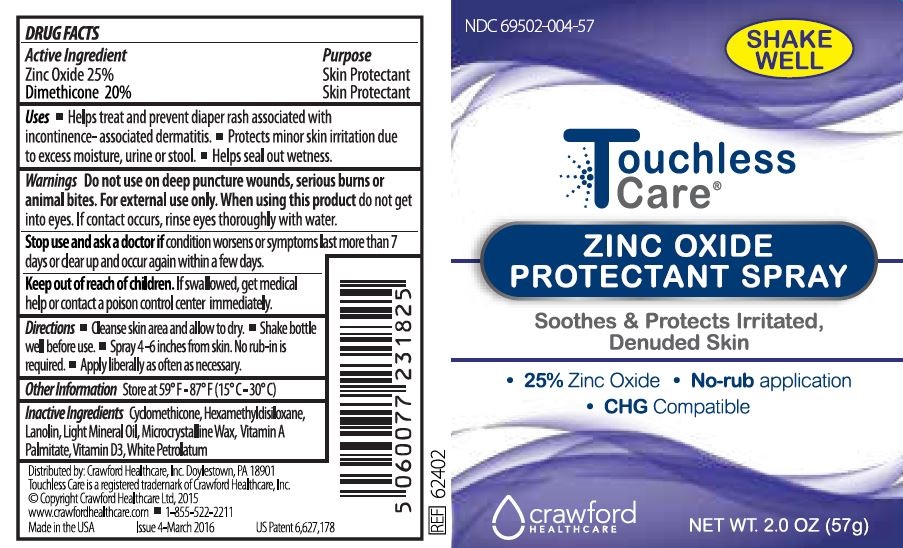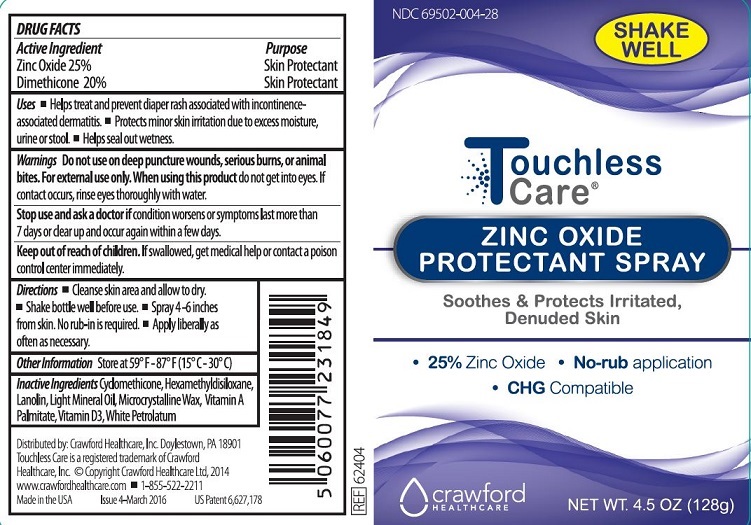 DRUG LABEL: Touchless Care ZINC OXIDE PROTECTANT
NDC: 69502-004 | Form: SPRAY
Manufacturer: Crawford Healthcare, Inc.
Category: otc | Type: HUMAN OTC DRUG LABEL
Date: 20220217

ACTIVE INGREDIENTS: DIMETHICONE 20 g/100 g; ZINC OXIDE 25 g/100 g
INACTIVE INGREDIENTS: CYCLOMETHICONE; HEXAMETHYLDISILOXANE; LANOLIN; MINERAL OIL; MICROCRYSTALLINE WAX; PETROLATUM; VITAMIN A PALMITATE; CHOLECALCIFEROL; .ALPHA.-TOCOPHEROL, DL-; CORN OIL

Touchless Care ZINC OXIDE PROTECTANT SPRAY

Active Ingredients

Zinc Oxide 25%

Dimethicone 20%

Purpose

Skin Protectant

Skin Protectant

Uses

- Helps treat and prevent diaper rash associated with incontinence associated dermatitis
- Protects minor skin irritation due to excess moisture, urine or stool
- Helps seal out wetness

Warnings

Do not use on deep puncture wounds, serious burns, or animal bites. For external use only. When using this product do not get into eyes. If contact occurs, rinse eyes thoroughly with water.

Stop use and ask a doctor if

condition worsens or symptoms last more than 7 days or clear up and occur again within a few days.

Keep out of reach of children

If swallowed, get medical help or contact a poison control center immediately.

Directions

- Cleanse skin area and allow to dry.
- Shake bottle well before use.
- Spray 4-6 inches from skin. No rub-in is required.
- Apply liberally as often as necessary.

Other Information

Store at 59ºF - 87ºF (15º C - 30º C)

Inactive Ingredients

Cyclomethicone, Hexamethyldisiloxane, Lanolin, Light Mineral Oil, Microcystalline Wax, Vitamin A Palmitate, Vitamin D3, White Petrolatum

Package Label

Touchless Care

ZINC OXIDE

PROTECTANT SPRAY

Soothes & Protects Irritated,

Denuded Skin

- 25% Zinc Oxide
- No-rub application
- CHG Compatible

Crawford

HEALTHCARE

NET WT. 4.5OZ (128g)